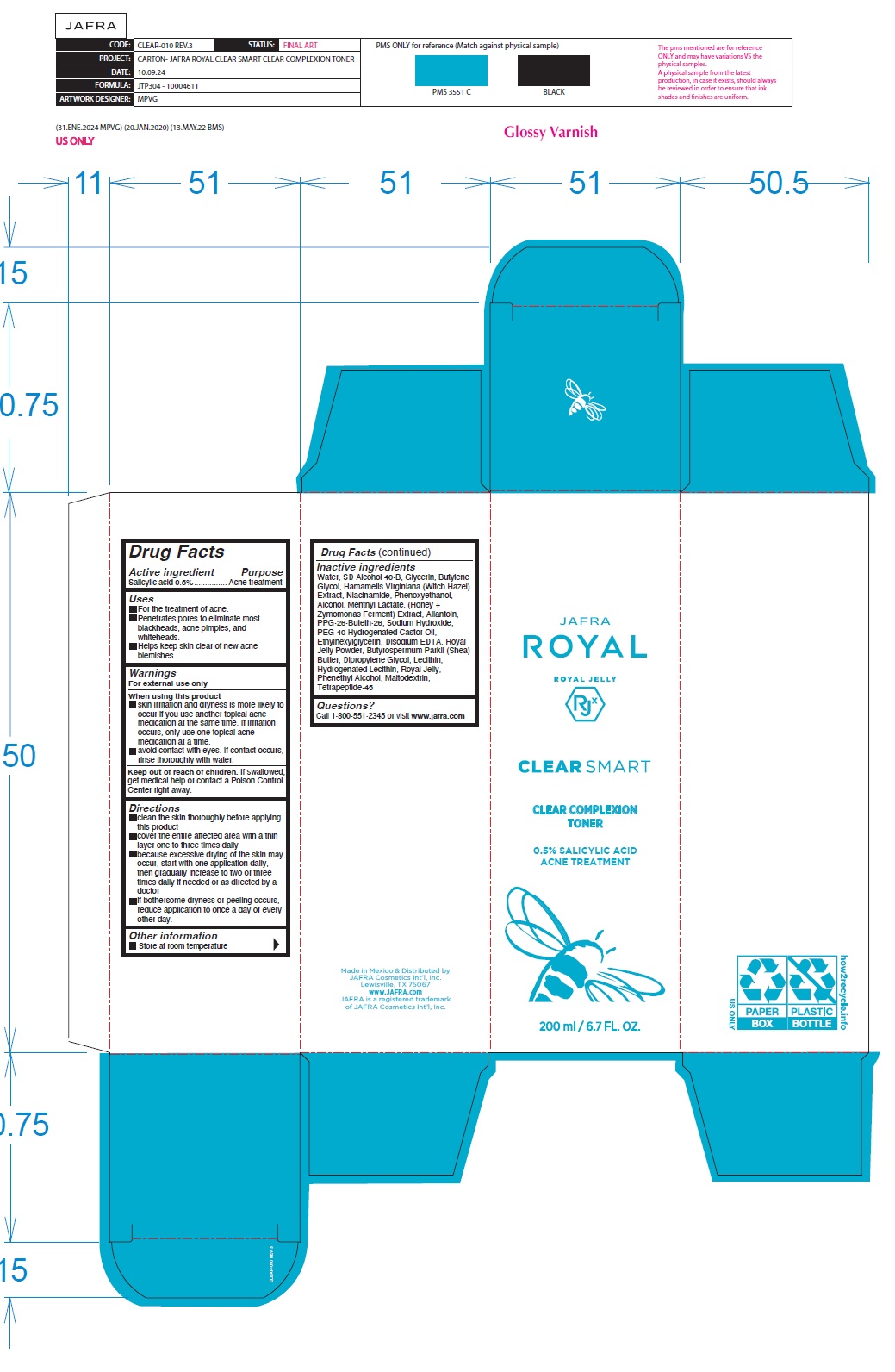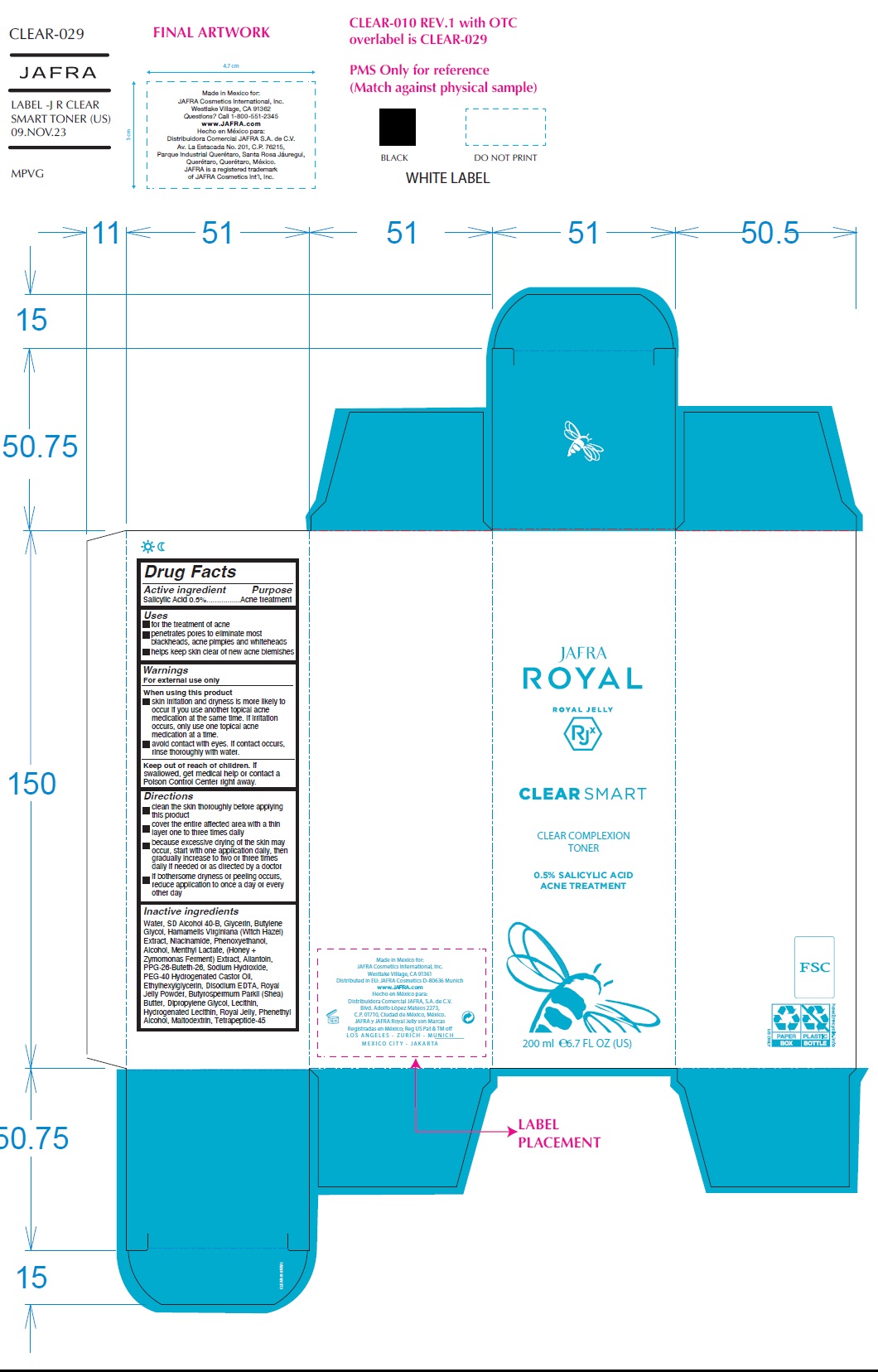 DRUG LABEL: Clear Smart Clear Complexion Toner
NDC: 68828-289 | Form: LIQUID
Manufacturer: Distribuidora Comercial Jafra, S.A. de C.V.
Category: otc | Type: HUMAN OTC DRUG LABEL
Date: 20251021

ACTIVE INGREDIENTS: SALICYLIC ACID 0.5 g/100 mL
INACTIVE INGREDIENTS: HONEY; NIACINAMIDE; HAMAMELIS VIRGINIANA TOP; MALTODEXTRIN; PPG-26-BUTETH-26; POLYOXYL 40 HYDROGENATED CASTOR OIL; PHENYLETHYL ALCOHOL; PHENOXYETHANOL; HYDROGENATED SOYBEAN LECITHIN; SODIUM HYDROXIDE; WATER; DIPROPYLENE GLYCOL; LECITHIN, SOYBEAN; MENTHYL LACTATE, (-)-; ETHYLHEXYLGLYCERIN; ROYAL JELLY; ALLANTOIN; BUTYLENE GLYCOL; EDETATE DISODIUM; SHEA BUTTER; GLYCERIN; ALCOHOL

Clear Smart Clear Complexion Toner

Active ingredient

Salicylic Acid 0.5%

Purpose

Acne treatment

Uses

- For the treatment of acne.
- Penetrates pores to eliminate most blackheads, acne pimples, and whiteheads.
- Helps keep skin clear of new acne blemishes.

Warnings

For external use only

When using this product

- skin irritation and dryness is more likely to occur if you use another topical acne medication at the same time. If irritation occurs, only use one topical acne medication at a time.
- avoid contact with eyes. If contact occurs, rinse thoroughly with water.

Keep out of reach of children.If swallowed, get medical help or contact a Poison Control Center right away.

Directions

- Clean the skin thoroughly before applying
- Cover the entire affected area with a thin layer one to three times daily
- Because excessive drying of the skin may occur, start with one application daily, then gradually increase to two or three times daily if needed or as directed by a doctor
- If bothersome dryness or peeling occurs, reduce application to once a day or every other day.

Other information

- Store at room temperature

Inactive ingredients

Water, SD Alcohol 40-B, Glycerin, Butylene Glycol, Hamamelis Virginiana (Witch Hazel) Extract, Niacinamide, Phenoxyethanol, Alcohol, Menthyl Lactate, (Honey + Zymomonas Ferment) Extract, Allantoin, PPG-26-Buteth-26, Sodium Hydroxide, PEG-40 Hydrogenated Castor Oil, Ethylhexylglycerin, Disodium EDTA, Royal Jelly Powder, Butyrospermum Parkii (Shea) Butter, Dipropylene Glycol, Lecithin, Hydrogenated Lecithin, Royal Jelly, Phenethyl Alcohol, Maltodextrin, Tetrapeptide-45

Questions?Call 1-800-551-2345 or visit www.jafra.com